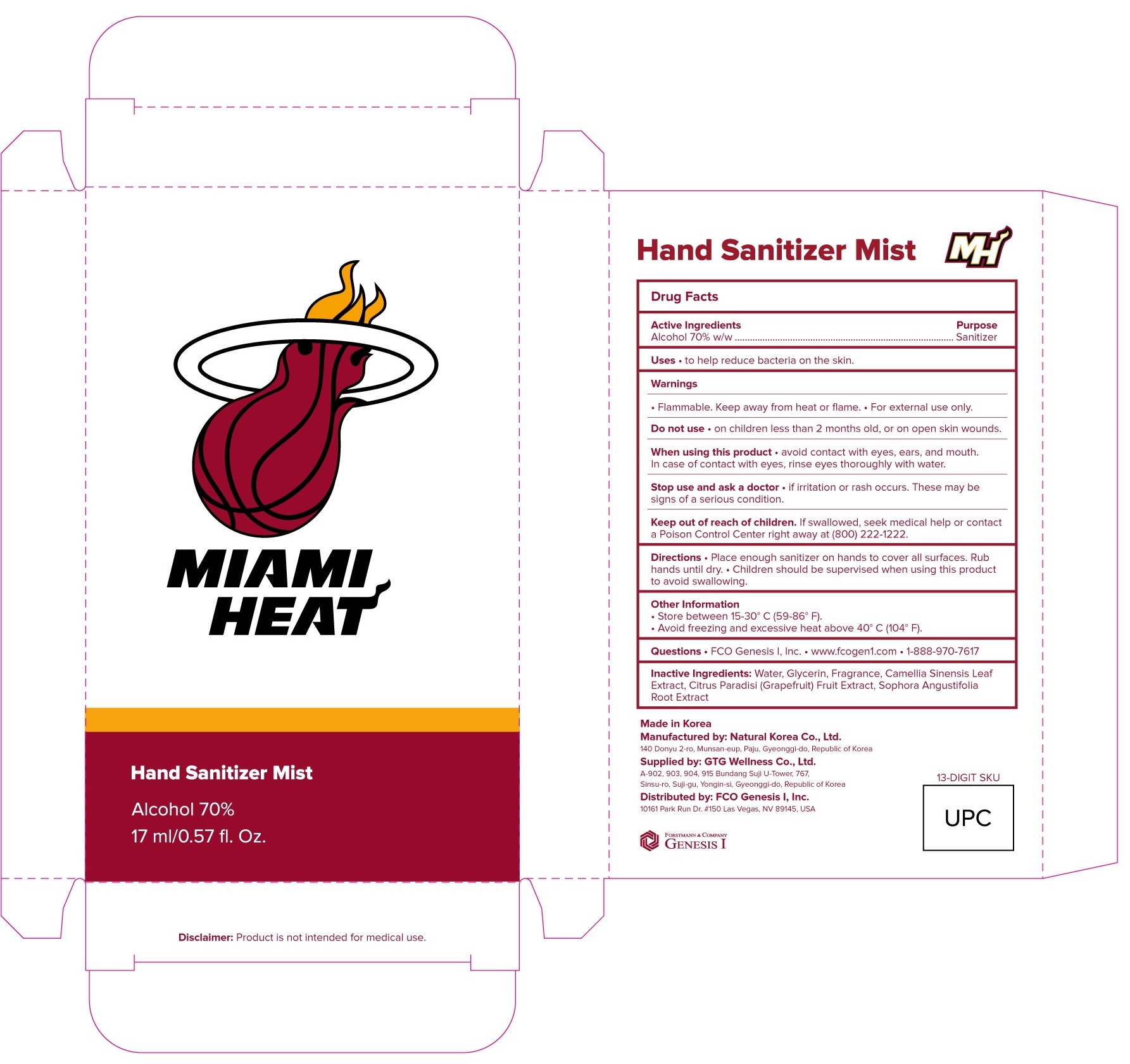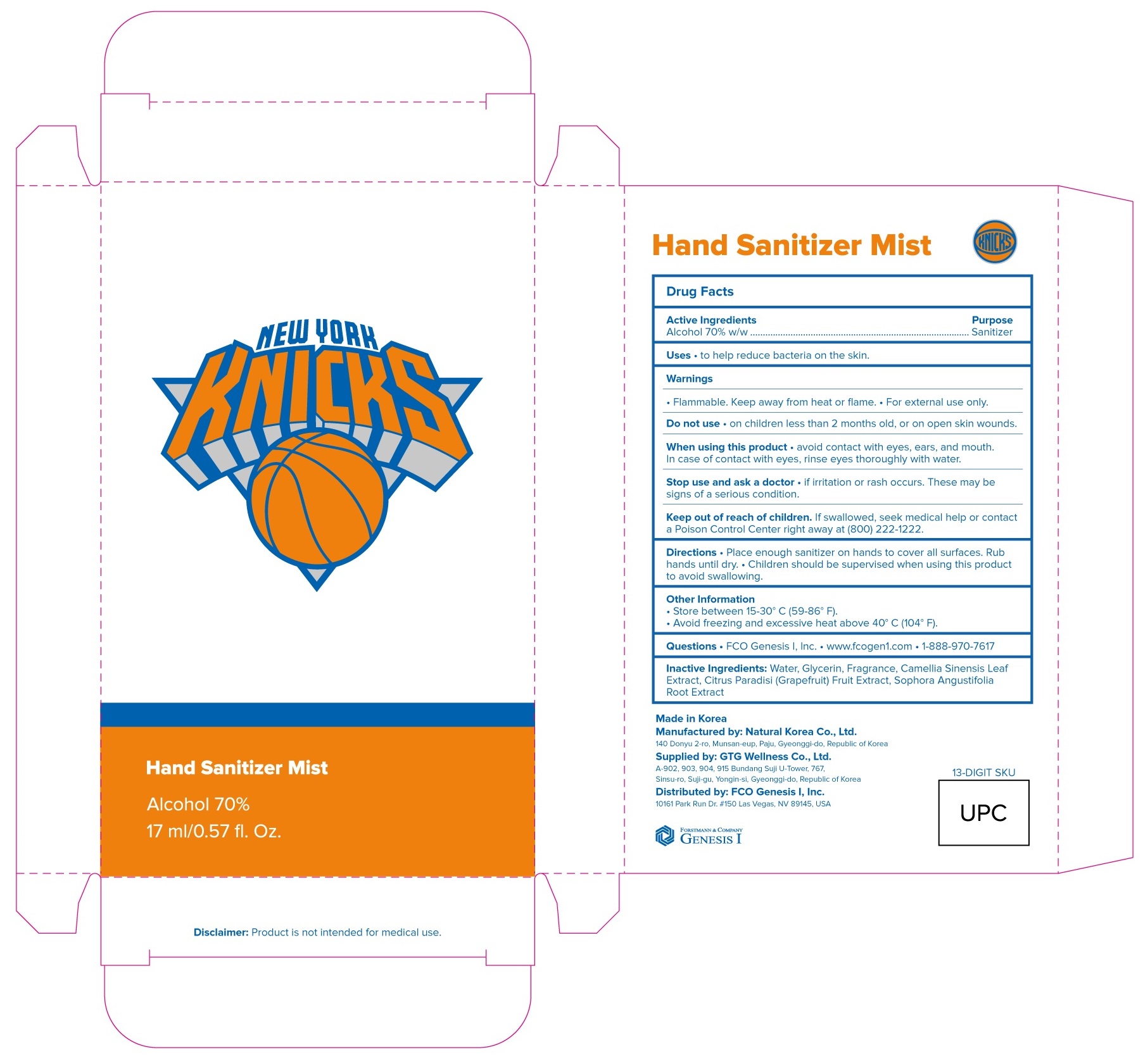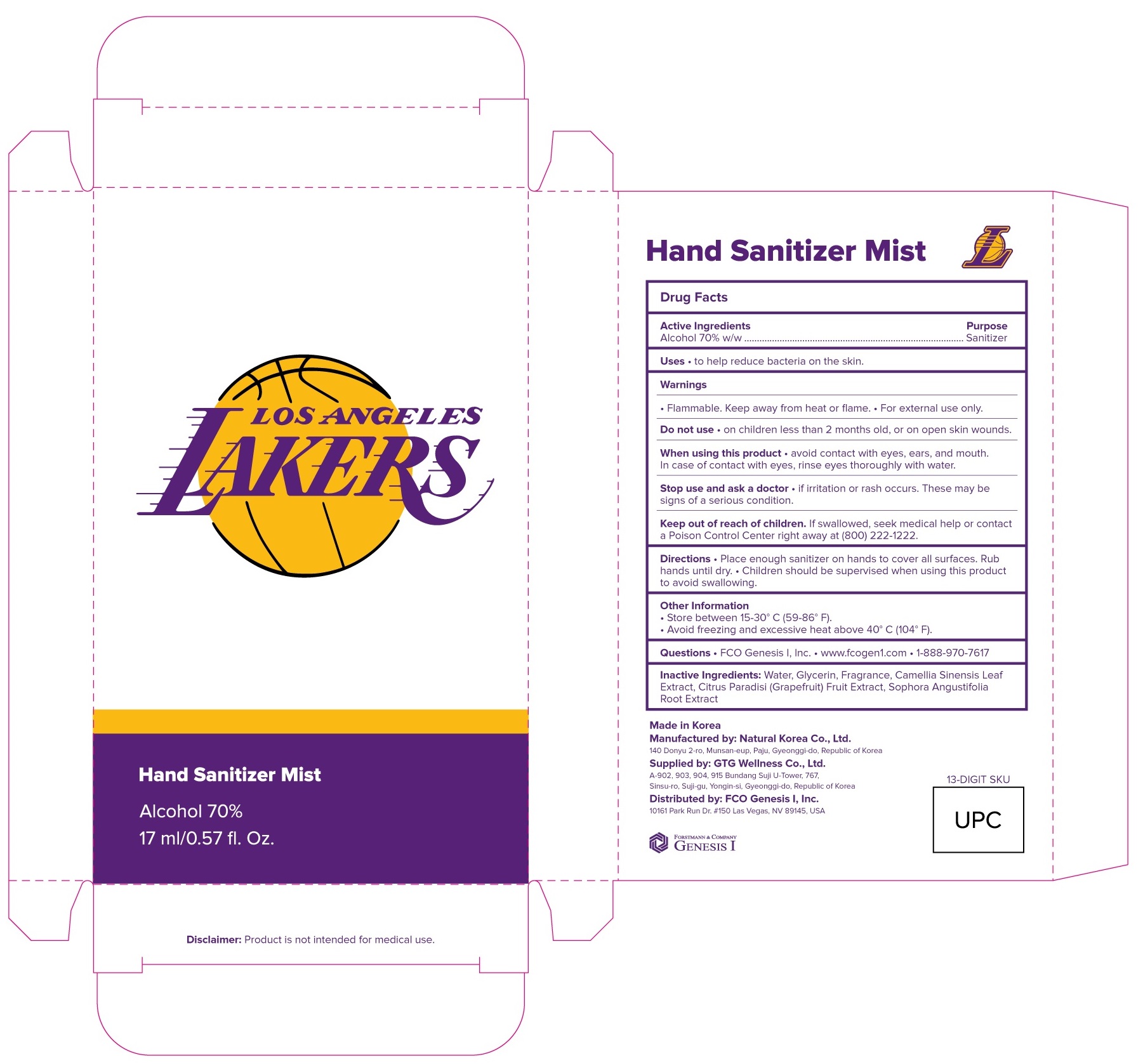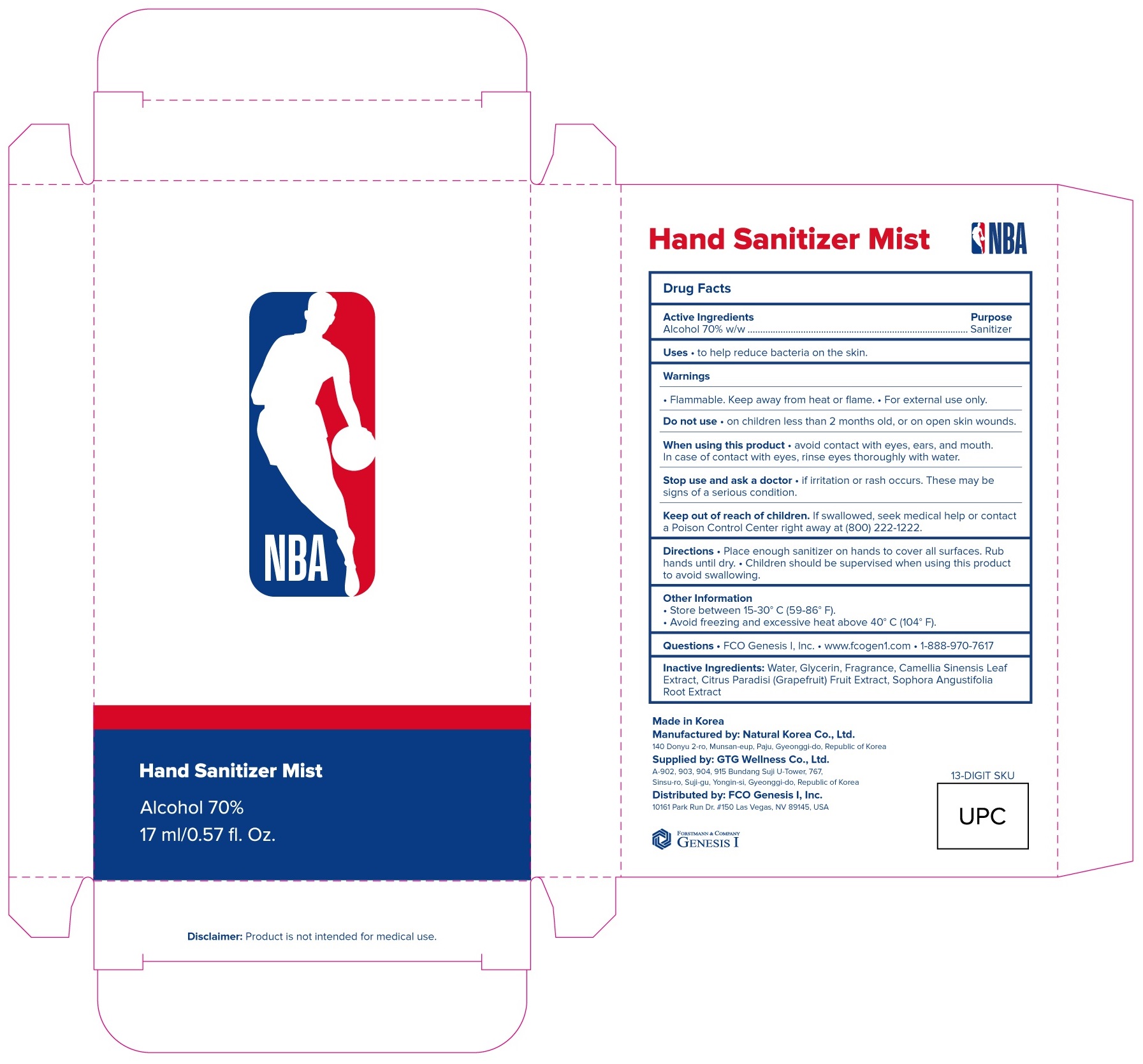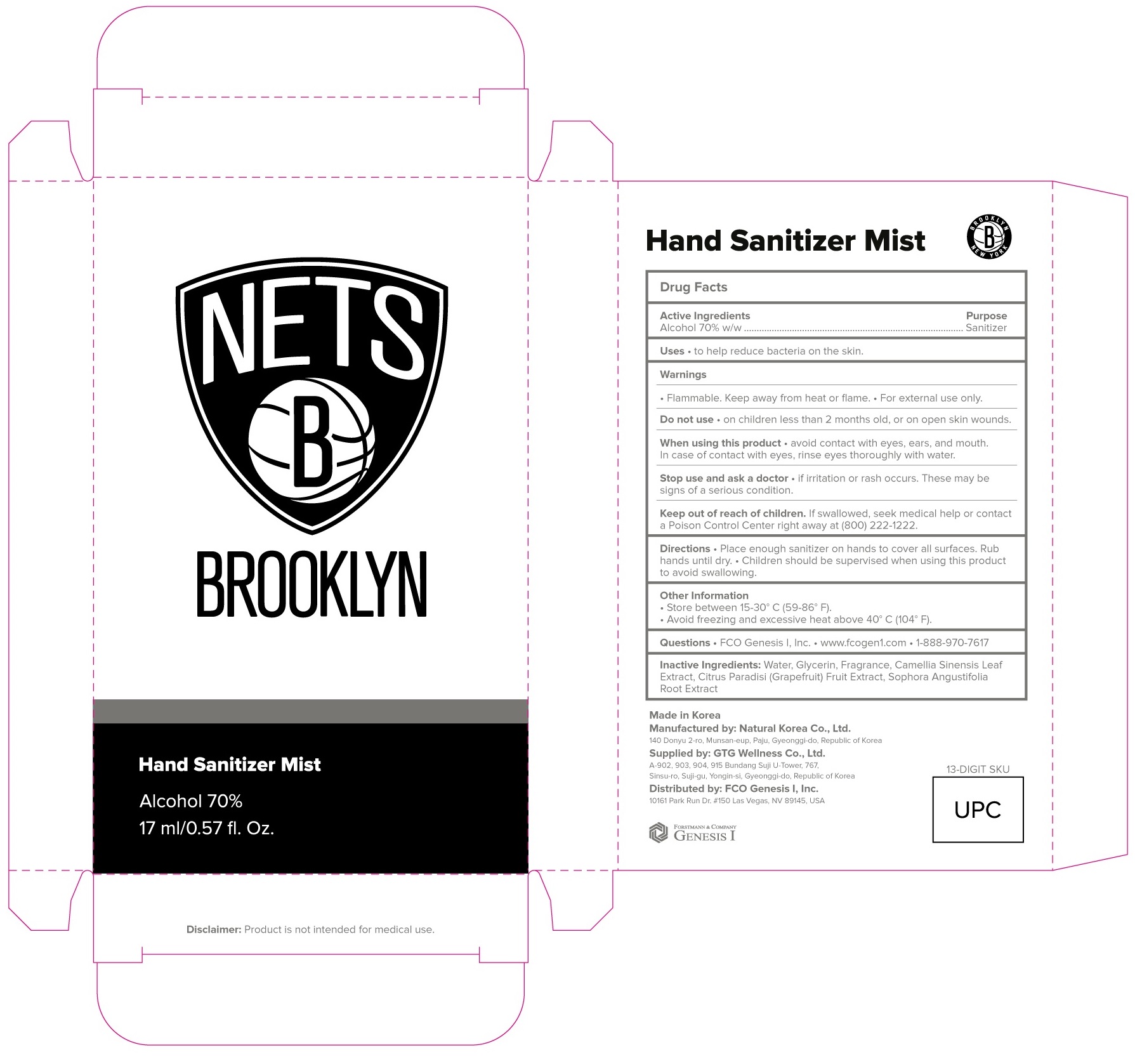 DRUG LABEL: Hand Sanitizer Mist
NDC: 71080-0023 | Form: SPRAY
Manufacturer: GTG WELLNESS CO., LTD.
Category: otc | Type: HUMAN OTC DRUG LABEL
Date: 20210514

ACTIVE INGREDIENTS: Alcohol 11.9 g/17 mL
INACTIVE INGREDIENTS: Water; Glycerin; GREEN TEA LEAF; GRAPEFRUIT; SOPHORA FLAVESCENS ROOT

ACTIVE INGREDIENT

Alcohol 70% w/w

INACTIVE INGREDIENTS

Water, Glycerin, Fragrance, Camellia Sinensis Leaf Extract, Citrus Paradisi (Grapefruit) Fruit Extract, Sophora Angustifolia Root Extract

PURPOSE

SANITIZER

WARNINGS

• Flammable. Keep away from heat and flame.
• For external use only.
--------------------------------------------------------------------------------------------------------
Do not use
• on children less than 2 months old, or on open skin wounds.

--------------------------------------------------------------------------------------------------------
When using this product • avoid contact with eyes, ears, and mouth. In case of contact with eyes, rinse eyes thoroughly with water.
--------------------------------------------------------------------------------------------------------
Stop use and ask a doctor • if irritation or rash occurs. These may be signs of a serious condition.

Keep out of reach of children. If swallowed, seek medical help or contact a Poison Control Center right away at (800) 222-1222.

Uses

■ to help reduce bacteria on skin.

Directions

■ Place enough sanitizer on hands to cover all surfaces.
■ Rub hands until dry.
■ Children should be supervised when using this product to avoid swallowing .

Other information

■ Store between 15-30°C (59-86°F)
■ Avoid freezing and excessive heat above 40°C (104°F)

Questions

• FCO Genesis I, Inc

• www.fcogen1.com

• 1-888-970-7617